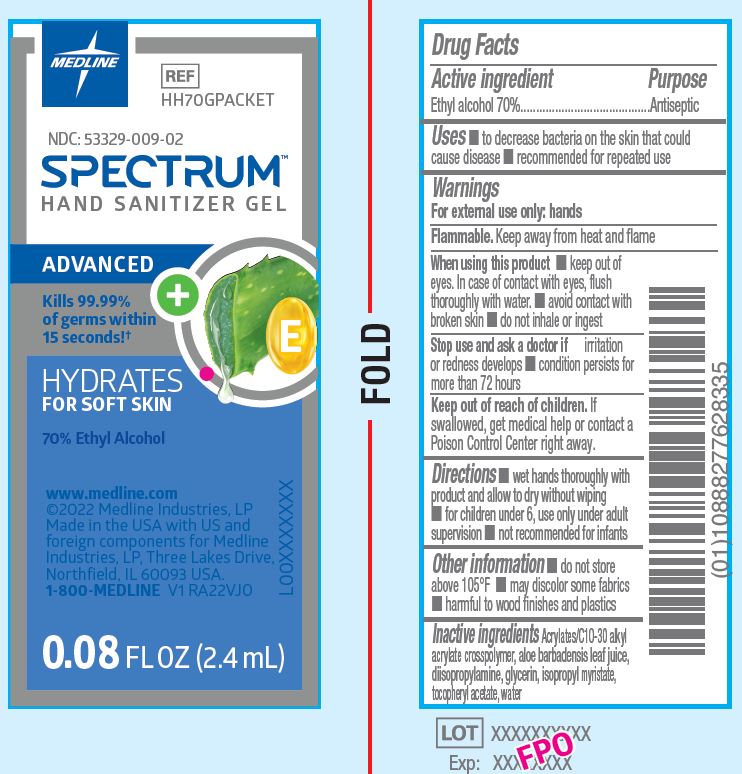 DRUG LABEL: Spectrum
NDC: 53329-009 | Form: GEL
Manufacturer: Medline Industries, LP
Category: otc | Type: HUMAN OTC DRUG LABEL
Date: 20260210

ACTIVE INGREDIENTS: ALCOHOL 70 g/100 mL
INACTIVE INGREDIENTS: DIISOPROPYLAMINE; ALPHA-TOCOPHEROL ACETATE; GLYCERIN; WATER; ALOE VERA LEAF; ISOPROPYL MYRISTATE; CARBOMER INTERPOLYMER TYPE A (ALLYL SUCROSE CROSSLINKED)

009 Spectrum Advanced 70% Packet

Active ingredient

Ethyl alcohol 70% v/v

Purpose

Antiseptic

Uses

- to decrease bacteria on the skin that could cause disease
- recommended for repeat use

Warnings

For external use only.

Flammable: keep away from heat and flame.

When using this product

- keep out of eyes. In case of contact with eyes, flush thoroughly with water.
- avoid contact with broken skin
- do not inhale or ingest

Stop use and ask a doctor if

- irritation or redness develops
- condition persists for more than 72 hours

Keep out of reach of children.

If swallowed, get medical help or contact a Poison Control Center right away.

Directions

- wet hands thoroughly with product and allow to dry without wiping
- for children under 6, use only under adult supervision
- not recommended for infants

Other information

- do not store above 105ºF
- may discolor some fabrics
- harmful to wood finishes and plastics

Inactive ingredients

Acrylates/C10-30 alkyl acrylate crosspolymer, aloe barbadensis leaf juice, diisopropylamine, glycerin, isopropyl myristate, tocopheryl acetate, water

Manufacturing Information

Manufactored for Medline industries, LP

Three Lakes Drive, Northfield, IL 60093 USA

Made in USA with US and Foreign components

www.medline.com

1-800-MEDLINE

REF: HH70GPACKET

V1 RA22VJO